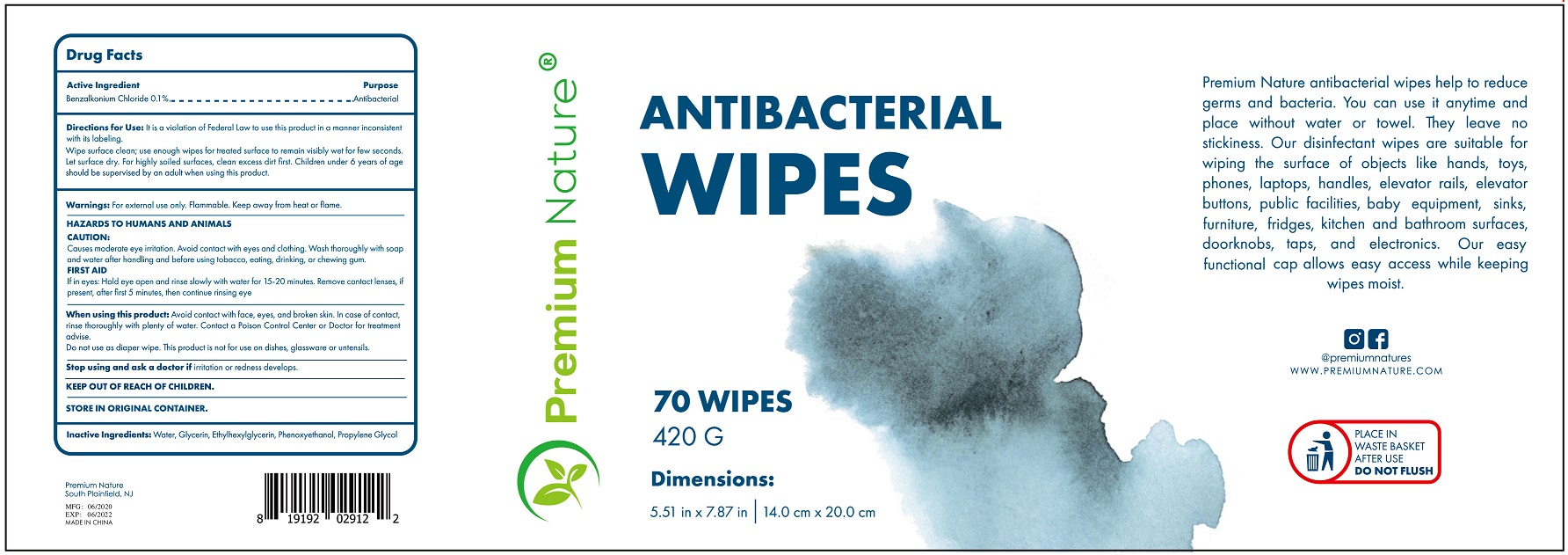 DRUG LABEL: Premium Nature Antibacterial Wipes
NDC: 77267-008 | Form: SWAB
Manufacturer: Ningbo Riway Daily Commodity Co., Ltd.
Category: otc | Type: HUMAN OTC DRUG LABEL
Date: 20200615

ACTIVE INGREDIENTS: BENZALKONIUM CHLORIDE 0.10 g/100 g
INACTIVE INGREDIENTS: water; GLYCERIN; ETHYLHEXYLGLYCERIN; PROPYLENE GLYCOL

Wipes

Active Ingredient

Benzalkonium Chloride 0.1%

Purpose

Antibacterial

USE

it is a violation of federal law to use this product in a manner inconsistent with its labeling.

Wipe surface clean; use enough wipes for treated surface to remain visibly wet for few seconds.

Let surface dry. For highly soiled surfaces, clean excess dirt first. Children under 6 years of age should be supervised by an adult when using this product.

Warning

For external use only. Flammable. Keep away from heat or flame.

HAZARDS TO HUMANS AND ANIMALS

CAUTION:

Cause moderote eye irritation, avoid contact with eyes and clothing. Wash thoroughly with soap and water after handling and before using tobacco, eating, drinking, or chewing gum.

FIRST AID

If in eyes: Hold eye open and rinse slowly with water for 15-20 minutes。 Remove contact lenses, if present, after first 5 inutes, then continue rinsing eye.

When using this product: Avoid contact with face, eyes, nd broken skin. In case of contact, rinse thoroughly with plenty of water. Contact a Poison Control Center or Doctor for treatment advise.

Do not use as diaper wipe. This product is not for use on dishes, glassware or untensils.

Stop using and ask a doctor if irritation or redness develops.

KEEP OUT OF REACH OF CHILDREN

If swallowed, get medical help or contact a Poison Contrl Center right away.

Directions

wipe surface clean.

Inactive ingredients

Water, Glycerin, Ehtylhexylglycerin, Phenoxyethanol, Propylene Glycol